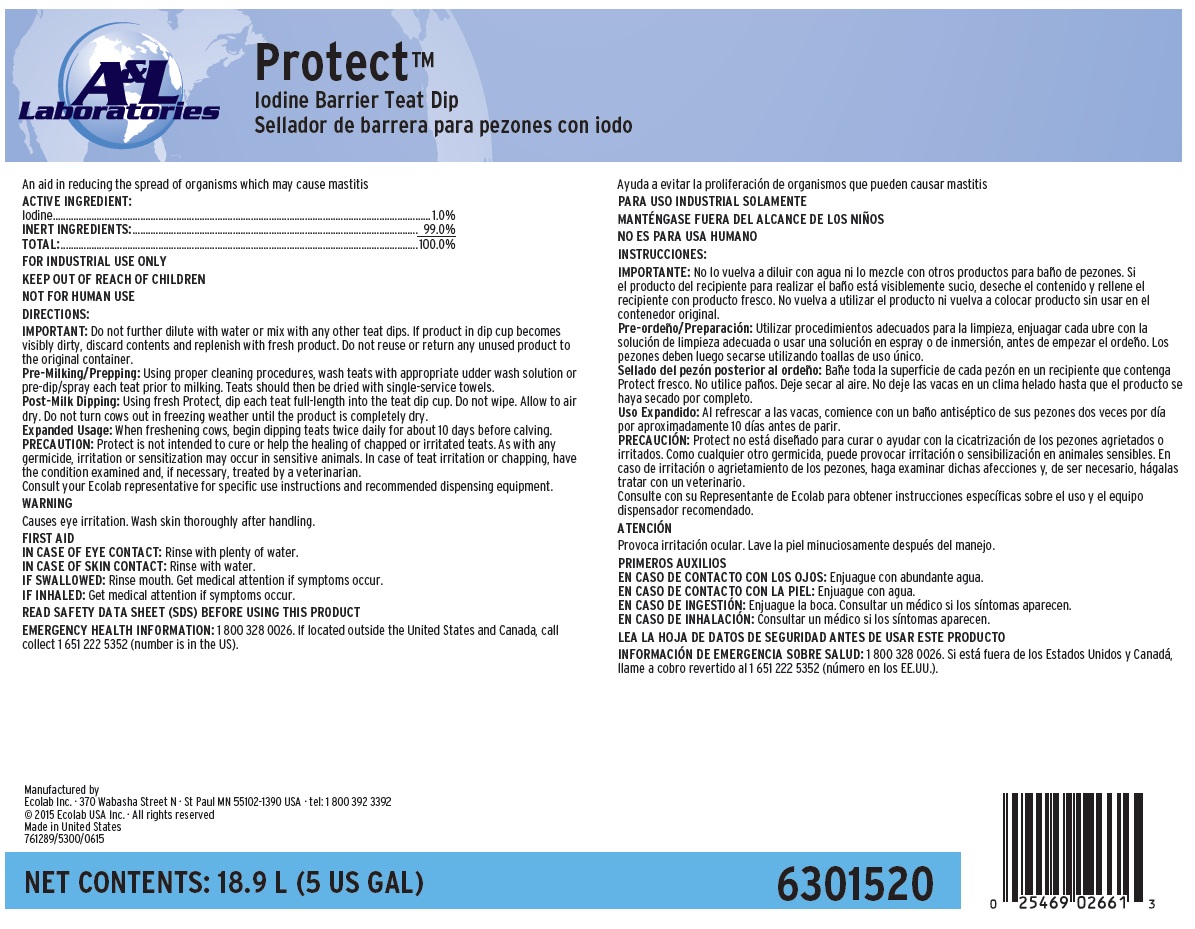 DRUG LABEL: Protect
NDC: 47593-548 | Form: SOLUTION
Manufacturer: Ecolab Inc.
Category: animal | Type: OTC ANIMAL DRUG LABEL
Date: 20251002

ACTIVE INGREDIENTS: IODINE 10 mg/1 mL
INACTIVE INGREDIENTS: WATER

WARNING

Causes eye irritation. Wash skin thoroughly after handling.

FOR INDUSTRIAL USE ONLY

KEEP OUT OF REACH OF CHILDREN

NOT FOR HUMAN USE

DIRECTIONS:

IMPORTANT: Do not further dilute with water or mix with any other teat dips. If product in dip cup becomes
visibly dirty, discard contents and replenish with fresh product. Do not reuse or return any unused product to
the original container.
Pre-Milking/Prepping: Using proper cleaning procedures, wash teats with appropriate udder wash solution or
pre-dip/spray each teat prior to milking. Teats should then be dried with single-service towels.
Post-Milk Dipping: Using fresh Protect, dip each teat full-length into the teat dip cup. Do not wipe. Allow to air
dry. Do not turn cows out in freezing weather until the product is completely dry.
Expanded Usage: When freshening cows, begin dipping teats twice daily for about 10 days before calving.
PRECAUTION: Protect is not intended to cure or help the healing of chapped or irritated teats. As with any
germicide, irritation or sensitization may occur in sensitive animals. In case of teat irritation or chapping, have
the condition examined and, if necessary, treated by a veterinarian.
Consult your Ecolab representative for specific use instructions and recommended dispensing equipment.

OTHER SAFETY INFORMATION

FIRST AID

IN CASE OF EYE CONTACT: Rinse with plenty of water.
IN CASE OF SKIN CONTACT: Rinse with water.
IF SWALLOWED: Rinse mouth. Get medical attention if symptoms occur.
IF INHALED: Get medical attention if symptoms occur.

READ SAFETY DATA SHEET (SDS) BEFORE USING THIS PRODUCT

EMERGENCY HEALTH INFORMATION: 1 800 328 0026. If located outside the United States and Canada, call
collect 1 651 222 5352 (number is in the US).

Representative label and principal display panel

A&L Laboratories

Protect™

Iodine Barrier Teat Dip

An aid in reducing the spread of organisms which may cause mastitis

ACTIVE INGREDIENT:
Iodine................................................................................................................................................... 1.0%
INERT INGREDIENTS:...................................................................................................................... 99.0%
TOTAL:............................................................................................................................................. 100.0%

Manufactured by
Ecolab Inc. · 370 Wabasha Street N · St Paul MN 55102-1390 USA · tel: 1 800 392 3392
© 2015 Ecolab USA Inc. · All rights reserved
Made in United States
761289/5300/0615

NET CONTENTS: 18.9L (5 US GAL) 6301520